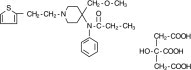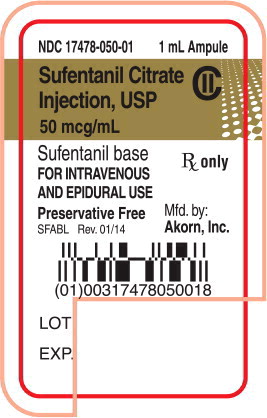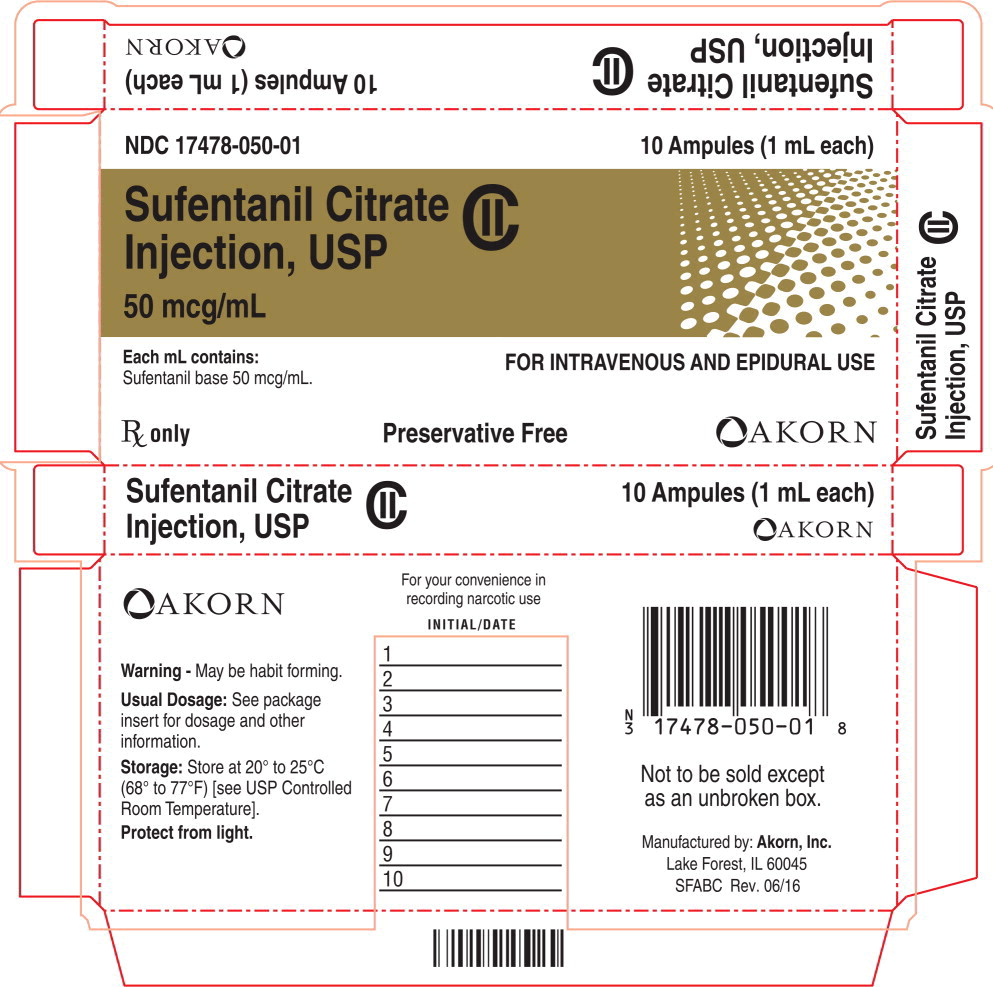 DRUG LABEL: Sufentanil Citrate
NDC: 17478-050 | Form: INJECTION
Manufacturer: Akorn
Category: prescription | Type: HUMAN PRESCRIPTION DRUG LABEL
Date: 20220914
DEA Schedule: CII

ACTIVE INGREDIENTS: Sufentanil Citrate 50 ug/1 mL
INACTIVE INGREDIENTS: Water

HIGHLIGHTS OF PRESCRIBING INFORMATION

These highlights do not include all the information needed to use SUFENTANIL CITRATE INJECTION, safely and effectively. See full prescribing information for SUFENTANIL CITRATE INJECTION.
Sufentanil Citrate Injection, for intravenous and epidural use, CII
Initial U.S. Approval: 1984

RECENT MAJOR CHANGES

Warnings and Precautions (5.2) | 10/2019

WARNING: ADDICTION, ABUSE, AND MISUSE

See full prescribing information for complete boxed warning.

- Sufentanil citrate injection exposes users to risks of addiction, abuse, and misuse, which can lead to overdose and death. Assess patient's risk before prescribing and monitor regularly for these behaviors and conditions. (5.1)

1 INDICATIONS AND USAGE

Sufentanil Citrate Injection is an opioid agonist indicated:

- as an analgesic adjunct in the maintenance of balanced general anesthesia in patients who are intubated and ventilated.
- as a primary anesthetic agent for the induction and maintenance of anesthesia with 100% oxygen in patients undergoing major surgical procedures, in patients who are intubated and ventilated, such as cardiovascular surgery or neurosurgical procedures in the sitting position, to provide favorable myocardial and cerebral oxygen balance or when extended postoperative ventilation is anticipated.
- for epidural administration as an analgesic combined with low dose (usually 12.5 mg per administration) bupivacaine usually during labor and vaginal delivery.

2 DOSAGE AND ADMINISTRATION

- Sufentanil Citrate Injection should be administered only by persons specifically trained in the use of intravenous anesthetics and management of the respiratory effects of potent opioids.
- Ensure that an opioid antagonist, resuscitative and intubation equipment, and oxygen are readily available (2.1).
- Individualize dosing based on factors such as age, body weight, physical status, underlying pathological condition, use of other drugs, type of anesthesia to be used, and the surgical procedure involved. (2.1)
- Initiate analgesic treatment with 1 to 2 mcg/kg intravenously. (2.2)
- Initiate epidural injection for labor and delivery at 10 to 15 mcg of Sufentanil administered with 10 mL bupivacaine 0.125% with or without epinephrine (2.3)

3 DOSAGE FORMS AND STRENGTHS

Solution for injection (sterile): eq. to 50 mcg/mL sufentanil base; 1 mL, 2 mL and 5 mL ampules (3)

4 CONTRAINDICATIONS

- Hypersensitivity to sufentanil. (4)

5 WARNINGS AND PRECAUTIONS

- Risks of Skeletal Muscle Rigidity and Skeletal Muscle Movement: Manage with neuromuscular blocking agent. See full prescribing information for more detail on managing these risks. (5.4)
- Life-Threatening Respiratory Depression in Patients with Chronic Pulmonary Disease or in Elderly, Cachectic, or Debilitated Patients: Monitor closely, particularly during initiation and titration. (5.2)
- Severe Cardiovascular Depression: Monitor during dosage initiation and titration. (5.6)
- Serotonin Syndrome: Potentially life-threatening condition could result from concomitant serotonergic drug administration. Discontinue Sufentanil Citrate Injection if serotonin syndrome is suspected. (5.7)
- Risks of Use in Patients with Increased Intracranial Pressure, Brain Tumors, or Head Injury: Monitor for sedation and respiratory depression. (5.9)

6 ADVERSE REACTIONS

Most common adverse reactions were apnea, rigidity, and bradycardia. (6)

To report SUSPECTED ADVERSE REACTIONS, contact Akorn, Inc. at 1-800-932-5676 or FDA at 1-800-FDA-1088 or www.fda.gov.medwatch.

7 DRUG INTERACTIONS

- Concomitant Use of CNS Depressants: May decrease pulmonary arterial pressure and may cause hypotension. See FPI for management instructions. For post-operative pain, start with the lowest effective dosage and monitor for potentiation of CNS depressant effects. (5.5, 7)
- Mixed Agonist/Antagonist and Partial Agonist Opioid Analgesics: Avoid use with Sufentanil Citrate Injection because they may reduce analgesic effect of Sufentanil Citrate Injection or precipitate withdrawal symptoms. (7)

8 USE IN SPECIFIC POPULATIONS

- Pregnancy: May cause fetal harm. (8.1)
- Lactation: Infants exposed to Sufentanil Citrate Injection through breast milk should be monitored for excess sedation and respiratory depression. (8.2)

FULL PRESCRIBING INFORMATION

WARNING: ADDICTION, ABUSE, AND MISUSE

See full prescribing information for complete boxed warning.

- Sufentanil citrate injection exposes users to risks of addiction, abuse, and misuse, which can lead to overdose and death. Assess patient's risk before prescribing and monitor regularly for these behaviors and conditions. (5.1)

1 INDICATIONS AND USAGE

Sufentanil Citrate Injection is indicated for intravenous administration in adults and pediatric patients:

- as an analgesic adjunct in the maintenance of balanced general anesthesia in patients who are intubated and ventilated.
- as a primary anesthetic agent for the induction and maintenance of anesthesia with 100% oxygen in patients undergoing major surgical procedures, in patients who are intubated and ventilated, such as cardiovascular surgery or neurosurgical procedures in the sitting position, to provide favorable myocardial and cerebral oxygen balance or when extended postoperative ventilation is anticipated.

Sufentanil Citrate Injection is indicated for epidural administration:

- as an analgesic combined with low dose (usually 12.5 mg per administration) bupivacaine usually during labor and vaginal delivery.

2 DOSAGE AND ADMINISTRATION

2.1 Important Dosage and Administration Instructions

Sufentanil Citrate Injection should be administered only by persons specifically trained in the use of intravenous or epidural anesthetics and management of the respiratory effects of potent opioids.

In patients administered high doses of Sufentanil Citrate Injection, it is essential that qualified personnel and adequate facilities are available for the management of postoperative respiratory depression.

For purposes of administering small volumes of Sufentanil Citrate Injection accurately, the use of a tuberculin syringe or equivalent is recommended.

- Ensure that an opioid antagonist, resuscitative and intubation equipment, and oxygen are readily available.
- Individualize dosage based on factors such as age, body weight, physical status, underlying pathological condition, use of other drugs, type of anesthesia to be used, and the surgical procedure involved.
- Monitor vital signs regularly.
- The selection of preanesthetic medications should be based upon the needs of the individual patient.
- The neuromuscular blocking agent selected should be compatible with the patient's condition, taking into account the hemodynamic effects of a particular muscle relaxant and the degree of skeletal muscle relaxation required.

As with other potent opioids, the respiratory depressant effect of sufentanil may persist longer than the measured analgesic effect. The total dose of all opioid agonists administered should be considered by the practitioner before ordering opioid analgesics during recovery from anesthesia.

If Sufentanil Citrate Injection is administered with a CNS depressant, become familiar with the properties of each drug, particularly each product's duration of action. In addition, when such a combination is used, fluids and other countermeasures to manage hypotension should be available [see Warnings and Precautions (5.5)].

Inspect parenteral drug products visually for particulate matter and discoloration prior to administration, whenever solution and container permit.

2.2 Intravenous use

Sufentanil Citrate may be administered intravenously by slow injection or infusion.

Adjunct to general anesthesia:

- Doses of up to 8 mcg/kg (see Table 1)
- Total Dosage Requirements Of 1 Mcg/Kg/Hr Or Less Are Recommended
- Dosage should be individualized and adjusted to remaining operative time anticipated.

Table 1: Adult Dosage Range Chart, Analgesic Component To General Anesthesia, Intravenous Use
Total dosage | Maintenance dosage
Duration of anesthesia 1 to 2 hours
Incremental or Infusion: 1 to 2 mcg/kg Approximately 75% or more of total sufentanil dosage may be administered prior to intubation by either slow injection or infusion titrated to individual patient response. Dosages in this range are generally administered with nitrous oxide/oxygen in patients undergoing general surgery in which endotracheal intubation and mechanical ventilation are required. | Incremental: 10 to 25 mcg (0.2 to 0.5 mL) may be administered in increments as needed when movement and/or changes in vital signs indicate surgical stress or lightening of analgesia. Supplemental dosages should be individualized and adjusted to remaining operative time anticipated. Infusion: Intermittent or continuous infusion as needed in response to signs of lightening of analgesia. In absence of signs of lightening of analgesia, infusion rates should always be adjusted downward until there is some response to surgical stimulation. Maintenance infusion rates should be adjusted based upon the induction dose of sufentanil so that the total dose does not exceed 1 mcg/kg/hr of expected surgical time.
Duration of anesthesia 2 to 8 hours
Incremental or Infusion: 2 to 8 mcg/kg Approximately 75% or less of the total calculated sufentanil dosage may be administered by slow injection or infusion prior to intubation, titrated to individual patient response. Dosages in this range are generally administered with nitrous oxide/oxygen in patients undergoing more complicated major surgical procedures in which endotracheal intubation and mechanical ventilation are required. At dosages in this range, sufentanil has been shown to provide some attenuation of sympathetic reflex activity in response to surgical stimuli, provide hemodynamic stability, and provide relatively rapid recovery. | Incremental: 10 to 50 mcg (0.2 to 1 mL) may be administered in increments as needed when movement and/or changes in vital signs indicate surgical stress or lightening of analgesia. Supplemental dosages should be individualized and adjusted to the remaining operative time anticipated. Infusion: Intermittent or continuous infusion as needed in response to signs of lightening of analgesia. In the absence of signs of lightening of analgesia, infusion rates should always be adjusted downward until there is some response to surgical stimulation. Maintenance infusion rates should be adjusted based upon the induction dose of sufentanil so that the total dose does not exceed 1 mcg/kg/hr of expected surgical time.

Induction And Maintenance Of Anesthesia

- As the primary anesthetic agent: doses ≥8 mcg/kg (see Dosage Range Chart, Table 2).
- Dosage should be titrated to individual patient response
- In children less than 12 years of age undergoing cardiovascular surgery: 10 to 25 mcg/kg administered with 100% oxygen
  - Supplemental dosages of up to 25 to 50 mcg are recommended for maintenance, based on response to initial dose and as determined by changes in vital signs indicating surgical stress or lightening of anesthesia.

Table 2: Dosage Range Chart, Induction and Maintenance of Anesthesia, Intravenous Use
Incremental or Infusion: 8 to 30 mcg/kg Generally administered as a slow injection, as an infusion, or as an injection followed by an infusion. Sufentanil with 100% oxygen and a muscle relaxant has been found to produce sleep at dosages ≥8 mcg/kg and to maintain a deep level of anesthesia without the use of additional anesthetic agents. The addition of N2O to these dosages will reduce systolic blood pressure. At dosages in this range of up to 25 mcg/kg, catecholamine release is attenuated. Dosages of 25 to 30 mcg/kg have been shown to block sympathetic response including catecholamine release. High doses are indicated in patients undergoing major surgical procedures, in which endotracheal intubation and mechanical ventilation are required, such as cardiovascular surgery and neurosurgery in the sitting position with maintenance of favorable myocardial and cerebral oxygen balance. Postoperative observation is essential and postoperative mechanical ventilation may be required at the higher dosage range due to extended postoperative respiratory depression. | Incremental: Depending on the initial dose, maintenance doses of 0.5 to 10 mcg/kg may be administered by slow injection in anticipation of surgical stress such as incision, sternotomy or cardiopulmonary bypass. Infusion: Sufentanil citrate may be administered by continuous or intermittent infusion as needed in response to signs of lightening of anesthesia. In the absence of lightening of anesthesia, infusion rates should always be adjusted downward until there is some response to surgical stimulation. The maintenance infusion rate for sufentanil should be based upon the induction dose so that the total dose for the procedure does not exceed 30 mcg/kg.

2.3 Epidural Use in Labor and Delivery

Proper placement of the needle or catheter in the epidural space should be verified before sufentanil citrate is injected to assure that unintentional intravascular or intrathecal administration does not occur. Unintentional intravascular injection of sufentanil could result in a potentially serious overdose, including acute truncal muscular rigidity and apnea. Unintentional intrathecal injection of the full sufentanil, bupivacaine epidural doses and volume could produce effects of high spinal anesthesia including prolonged paralysis and delayed recovery.

- Sufentanil should be administered by slow injection. Respiration should be closely monitored following each administration of an epidural injection of sufentanil.
- If analgesia is inadequate, the placement and integrity of the catheter should be verified prior to the administration of any additional epidural medications.

Dosage for Labor and Delivery

- 10 to 15 mcg administered with 10 mL bupivacaine 0.125% with or without epinephrine.
- Sufentanil and bupivacaine should be mixed together before administration.
- Doses can be repeated twice (for a total of three doses) at not less than one-hour intervals until delivery.

3 DOSAGE FORMS AND STRENGTHS

Sufentanil Citrate Injection, USP 50 mcg/mL (equivalent to 50 mcg/mL sufentanil base).

4 CONTRAINDICATIONS

Sufentanil Citrate Injection is contraindicated in patients with:

- Hypersensitivity to sufentanil (e.g., anaphylaxis) [see Adverse Reactions (6.2)]

5 WARNINGS AND PRECAUTIONS

5.1 Addiction, Abuse, and Misuse

Sufentanil Citrate Injection contains sufentanil, a Schedule II controlled substance. As an opioid, Sufentanil Citrate Injection exposes users to the risks of addiction, abuse, and misuse [see Drug Abuse and Dependence (9)].

Opioids are sought by drug abusers and people with addiction disorders and are subject to criminal diversion. Consider these risks when handling Sufentanil Citrate Injection. Strategies to reduce these risks include proper product storage and control practices for a C-II drug. Contact local state professional licensing board or state controlled substances authority for information on how to prevent and detect abuse or diversion of this product.

5.2 Life-Threatening Respiratory Depression

Serious, life-threatening, or fatal respiratory depression has been reported with the use of opioids, even when used as recommended. Respiratory depression, if not immediately recognized and treated, may lead to respiratory arrest and death. Sufentanil Citrate Injection should be administered only by persons specifically trained in the use of anesthetic drugs and the management of the respiratory effects of potent opioids, including respiration and cardiac resuscitation of patients in the age group being treated. Such training must include the establishment and maintenance of a patent airway and assisted ventilation. Adequate facilities should be available for postoperative monitoring and ventilation of patients administered anesthetic doses of Sufentanil Citrate Injection. It is essential that these facilities be fully equipped to handle all degrees of respiratory depression. Management of respiratory depression may include close observation, supportive measures, and use of opioid antagonists, depending on the patient's clinical status [see Overdosage (10)]. Carbon dioxide (CO2) retention from opioid-induced respiratory depression can exacerbate the sedating effects of opioids.

As with other potent opioids, the respiratory depressant effect of Sufentanil Citrate Injection may persist longer than the measured analgesic effect. The total dose of all opioid agonists administered should be considered by the practitioner before ordering opioid analgesics during recovery from anesthesia.

Certain forms of conduction anesthesia, such as spinal anesthesia and some epidural anesthetics, can alter respiration by blocking intercostal nerves [see Clinical Pharmacology (12.2)] Sufentanil Citrate Injection can also alter respiration. Therefore, when Sufentanil Citrate Injection is used to supplement these forms of anesthesia, the anesthetist should be familiar with the physiological alterations involved, and be prepared to manage them in the patients selected for these forms of anesthesia.

Patients with significant chronic obstructive pulmonary disease or cor pulmonale, and those with a substantially decreased respiratory reserve, hypoxia, hypercapnia, or pre-existing respiratory depression are at increased risk of decreased respiratory drive including apnea, even at recommended dosages of Sufentanil Citrate Injection. Elderly, cachectic, or debilitated patients may have altered pharmacokinetics or altered clearance compared to younger, healthier patients resulting in greater risk for respiratory depression.

Monitor such patients closely including vital signs, particularly when initiating and titrating Sufentanil Citrate Injection and when Sufentanil Citrate Injection is given concomitantly with other drugs that depress respiration. To reduce the risk of respiratory depression, proper dosing and titration of Sufentanil Citrate Injection are essential [see Dosage and Administration (2.1)].

Opioids can cause sleep-related breathing disorders including central sleep apnea (CSA) and sleep-related hypoxemia. Opioid use increases the risk of CSA in a dose-dependent fashion. In patients who present with CSA, consider decreasing the opioid dosage using best practices for opioid taper [see Dosage and Administration (2.1)].

5.3 Risks of Concomitant Use or Discontinuation of Cytochrome P450 3A4 Inhibitors and Inducers

Concomitant use of Sufentanil Citrate Injection with a CYP3A4 inhibitor, such as macrolide antibiotics (e.g., erythromycin), azole-antifungal agents (e.g., ketoconazole), and protease inhibitors (e.g., ritonavir), may increase plasma concentrations of sufentanil and prolong opioid adverse reactions, which may exacerbate fatal respiratory depression [see Warnings and Precautions (5.2)], particularly when an inhibitor is added after a stable dose of Sufentanil Citrate Injection is achieved. Similarly, discontinuation of a CYP3A4 inducer, such as rifampin, carbamazepine, and phenytoin, in Sufentanil Citrate Injection-treated patients may increase sufentanil plasma concentrations and prolong opioid adverse reactions. When using Sufentanil Citrate Injection with CYP3A4 inhibitors or discontinuing CYP3A4 inducers in Sufentanil Citrate Injection-treated patients, monitor patients closely at frequent intervals and consider dosage reduction of Sufentanil Citrate Injection [see Dosage and Administration (2.1), Drug Interactions (7)].

Concomitant use of Sufentanil Citrate Injection with CYP3A4 inducers or discontinuation of an CYP3A4 inhibitor could result in lower than expected sufentanil plasma concentrations, and decrease efficacy. When using Sufentanil Citrate Injection with CYP3A4 inducers or discontinuing CYP3A4 inhibitors, monitor patients closely at frequent intervals and consider increasing the Sufentanil Citrate Injection dosage [see Dosage and Administration (2.1), Drug Interactions (7)].

5.4 Risks of Muscle Rigidity and Skeletal Muscle Movement

Intravenous administration or unintentional intravascular injection during epidural administration of Sufentanil Citrate Injection may cause muscle rigidity, particularly involving the muscles of respiration. The incidence and severity of muscle rigidity is dose related. These effects are related to the dose and speed of injection. Administration of sufentanil may produce muscular rigidity with a more rapid onset of action than that seen with fentanyl. Skeletal muscle rigidity also has been reported to occur or recur infrequently in the extended postoperative period usually following high dose administration. In addition, skeletal muscle movements of various groups in the extremities, neck, and external eye have been reported during induction of anesthesia with Sufentanil Citrate Injection; these reported movements have, on rare occasions, been strong enough to pose patient management problems.

The incidence of skeletal muscle rigidity can be reduced by: 1) administration of up to 1/4 of the full paralyzing dose of a non-depolarizing neuromuscular blocking agent just prior to administration of sufentanil at dosages of up to 8 mcg/kg, 2) administration of a full paralyzing dose of a neuromuscular blocking agent following loss of consciousness when sufentanil is used in anesthetic dosages (above 8 mcg/kg) titrated by slow intravenous infusion, or, 3) simultaneous administration of sufentanil and a full paralyzing dose of a neuromuscular blocking agent when sufentanil is used in rapidly administered anesthetic dosages (above 8 mcg/kg).

The neuromuscular blocking agents used should be compatible with the patient's cardiovascular status. The hemodynamic effects and degree of skeletal muscle relaxation required should be considered in the selection of a neuromuscular blocking agent. High doses of pancuronium may produce increases in heart rate during sufentanil-oxygen anesthesia. Bradycardia and hypotension have been reported with other muscle relaxants during sufentanil-oxygen anesthesia; this effect may be more pronounced in the presence of calcium channel and/or beta-blockers. Muscle relaxants with no clinically significant effect on heart rate (at recommended doses) would not counteract the vagotonic effect of sufentanil, therefore a lower heart rate would be expected. Rare reports of bradycardia associated with the concomitant use of succinylcholine and sufentanil have been reported.

5.5 Risks from Concomitant Use with Benzodiazepines or Other CNS Depressants

When benzodiazepines or other CNS depressants are used with Sufentanil Citrate Injection, pulmonary arterial pressure may be decreased. This fact should be considered by those who conduct diagnostic and surgical procedures where interpretation of pulmonary arterial pressure measurements might determine final management of the patient. When high dose or anesthetic dosages of Sufentanil Citrate Injection are employed, even relatively small dosages of diazepam may cause cardiovascular depression.

When Sufentanil Citrate Injection is used with CNS depressants, hypotension can occur. If it occurs, consider the possibility of hypovolemia and manage with appropriate parenteral fluid therapy. When operative conditions permit, consider repositioning the patient to improve venous return to the heart. Exercise care in moving and repositioning of patients because of the possibility of orthostatic hypotension. If volume expansion with fluids plus other countermeasures do not correct hypotension, consider administration of pressor agents other than epinephrine. Epinephrine may paradoxically decrease blood pressure in patients treated with a neuroleptic that blocks alpha adrenergic activity.

Profound sedation, respiratory depression, coma, and death may result from the concomitant use of Sufentanil Citrate Injection with benzodiazepines or other CNS depressants (e.g., nonbenzodiazepine sedatives/hypnotics, anxiolytics, tranquilizers, muscle relaxants, general anesthetics, antipsychotics, other opioids, alcohol).

If the decision is made to manage postoperative pain with Sufentanil Citrate Injection concomitantly with a benzodiazepine or other CNS depressant, start dosing with the lowest effective dosage and titrate based on clinical response. Follow patients closely for signs and symptoms of respiratory depression, sedation, and hypotension. Fluids or other measures to counter hypotension should be available. [see Drug Interactions (7)]

5.6 Severe Cardiovascular Depression

Sufentanil Citrate Injection may cause severe bradycardia, severe hypotension including orthostatic hypotension, and syncope. There is increased risk in patients whose ability to maintain blood pressure has already been compromised by a reduced blood volume or concurrent administration of certain CNS depressant drugs (e.g., phenothiazines or general anesthetics) [see Drug Interactions (7)]. In patients with circulatory shock, Sufentanil Citrate Injection may cause vasodilation that can further reduce cardiac output and blood pressure. Monitor these patients for signs of hypotension after initiating or titrating the dosage of Sufentanil Citrate Injection.

5.7 Serotonin Syndrome with Concomitant Use of Serotonergic Drugs

Cases of serotonin syndrome, a potentially life-threatening condition, have been reported during concomitant use of Sufentanil Citrate Injection with serotonergic drugs. Serotonergic drugs include selective serotonin reuptake inhibitors (SSRIs), serotonin and norepinephrine reuptake inhibitors (SNRIs), tricyclic antidepressants (TCAs), triptans, 5-HT3 receptor antagonists, drugs that affect the serotonergic neurotransmitter system (e.g., mirtazapine, trazodone, tramadol), certain muscle relaxants (i.e., cyclobenzaprine, metaxalone), and drugs that impair metabolism of serotonin (including MAO inhibitors, both those intended to treat psychiatric disorders and also others, such as linezolid and intravenous methylene blue) [see Drug Interactions (7)]. This may occur within the recommended dosage range.

Serotonin syndrome symptoms may include mental status changes (e.g., agitation, hallucinations, coma), autonomic instability (e.g., tachycardia, labile blood pressure, hyperthermia), neuromuscular aberrations (e.g., hyperreflexia, incoordination, rigidity), and/or gastrointestinal symptoms (e.g., nausea, vomiting, diarrhea). The onset of symptoms generally occurs within several hours to a few days of concomitant use, but may occur later than that. Discontinue Sufentanil Citrate Injection if serotonin syndrome is suspected.

5.8 Risks due to Improper Epidural Injection

Proper placement of the needle or catheter in the epidural space should be verified before sufentanil is injected to assure that unintentional intravascular or intrathecal administration does not occur. Unintentional intravascular injection of sufentanil could result in a potentially serious overdose, including acute truncal muscular rigidity and apnea. Unintentional intrathecal injection of the full sufentanil/ bupivacaine epidural doses and volume could produce effects of high spinal anesthesia including prolonged paralysis and delayed recovery. If analgesia is inadequate, the placement and integrity of the catheter should be verified prior to the administration of any additional epidural medications. Sufentanil should be administered epidurally by slow injection.

5.9 Risks of Use in Patients with Increased Intracranial Pressure, Brain Tumors, or Head Injury

In patients who may be susceptible to the intracranial effects of CO2 retention (e.g., those with evidence of increased intracranial pressure or brain tumors), Sufentanil Citrate Injection may reduce respiratory drive, and the resultant CO2 retention can further increase intracranial pressure. Monitor such patients for signs of increasing intracranial pressure.

5.10 Risks of Use in Patients with Gastrointestinal Conditions

Sufentanil may cause spasm of the sphincter of Oddi. Opioids may cause increases in serum amylase. Monitor patients with biliary tract disease, including acute pancreatitis for worsening symptoms.

5.11 Increased Risk of Seizures in Patients with Seizure Disorders

Sufentanil may increase the frequency of seizures in patients with seizure disorders, and may increase the risk of seizures occurring in other clinical settings associated with seizures. Monitor patients with a history of seizure disorders for worsened seizure control during Sufentanil Citrate Injection therapy.

5.12 Risks of Driving and Operating Machinery

Sufentanil Citrate Injection may impair the mental or physical abilities needed to perform potentially hazardous activities such as driving a car or operating machinery. Warn patients not to drive or operate dangerous machinery after Sufentanil Citrate Injection administration.

6 ADVERSE REACTIONS

The following serious adverse reactions are described, or described in greater detail, in other sections:

- Addiction, Abuse, and Misuse [see Warnings and Precautions (5.1)]
- Life-Threatening Respiratory Depression [see Warnings and Precautions (5.2)]
- Skeletal Muscle Rigidity and Skeletal Muscle Movement [see Warnings and Precautions (5.4)]
- Interactions with Benzodiazepines or Other CNS Depressants [see Warnings and Precautions (5.5)
- Severe Cardiovascular Depression [see Warnings and Precautions (5.6)]
- Serotonin Syndrome [see Warnings and Precautions (5.7)]
- Gastrointestinal Adverse Reactions [see Warnings and Precautions (5.10)]
- Seizures [see Warnings and Precautions (5.11)]

6.1 Clinical Trials Experience

Because clinical trials are conducted under widely varying conditions, adverse reaction rates observed in the clinical trials of a drug cannot be directly compared to rates in the clinical trials of another drug and may not reflect the rates observed in practice.

Epidural Use in Labor and Delivery

Epidural sufentanil was tested in 340 patients in two (one single-center and one multicenter) double-blind, parallel studies. Doses ranged from 10 to 15 mcg sufentanil and were delivered in a 10 mL volume of 0.125% bupivacaine with and without epinephrine 1:200,000. In all cases sufentanil was administered following a dose of local anesthetic to test proper catheter placement. Since epidural opioids and local anesthetics potentiate each other, these results may not reflect the dose or efficacy of epidural sufentanil by itself.

Individual doses of 10 to 15 mcg sufentanil plus bupivacaine 0.125% with epinephrine provided analgesia during the first stage of labor with a duration of 1 to 2 hours. Onset was rapid (within 10 minutes). Subsequent doses (equal dose) tended to have shorter duration. Analgesia was profound (complete pain relief) in 80% to 100% of patients and a 25% incidence of pruritus was observed. The duration of initial doses of sufentanil plus bupivacaine with epinephrine is approximately 95 minutes, and of subsequent doses, 70 minutes.

There are insufficient data to critically evaluate neonatal neuromuscular and adaptive capacity following recommended doses of maternally administered epidural sufentanil with bupivacaine. However, if larger than recommended doses are used for combined local and systemic analgesia, e.g. after administration of a single dose of 50 mcg epidural sufentanil during delivery, then impaired neonatal adaption to sound and light can be detected for 1 to 4 hours and if a dose of 80 mcg is used impaired neuromuscular coordination can be detected for more than 4 hours.

6.2 Postmarketing Experience

The following adverse reactions have been identified during post approval use of sufentanil. Because these reactions are reported voluntarily from a population of uncertain size, it is not always possible to reliably estimate their frequency or establish a causal relationship to drug exposure.

Serotonin syndrome: Cases of serotonin syndrome, a potentially life-threatening condition, have been reported during concomitant use of opioids with serotonergic drugs.

Adrenal insufficiency: Cases of adrenal insufficiency have been reported with opioid use, more often following greater than one month of use.

Anaphylaxis: Anaphylaxis has been reported with ingredients contained in Sufentanil Citrate Injection.

Androgen deficiency: Cases of androgen deficiency have occurred with chronic use of opioids [see Clinical Pharmacology (12.2)].

7 DRUG INTERACTIONS

Table 3 includes clinically significant drug interactions with Sufentanil Citrate Injection.

Table 3: Clinically Significant Drug Interactions with Sufentanil Citrate Injection
Inhibitors of CYP3A4
Clinical Impact: | The concomitant use of Sufentanil Citrate Injection and CYP3A4 inhibitors can increase the plasma concentration of sufentanil, resulting in increased or prolonged opioid effects, particularly when an inhibitor is added after a stable dose of Sufentanil Citrate Injection is achieved [see Warnings and Precautions (5.4)]. After stopping a CYP3A4 inhibitor, as the effects of the inhibitor decline, the sufentanil plasma concentration will decrease [see Clinical Pharmacology (12.3)], resulting in decreased opioid efficacy or a withdrawal syndrome in patients who had developed physical dependence to sufentanil.
Intervention: | If concomitant use is necessary, consider dosage reduction of Sufentanil Citrate Injection until stable drug effects are achieved. Monitor patients for respiratory depression and sedation at frequent intervals. If a CYP3A4 inhibitor is discontinued, consider increasing the Sufentanil Citrate Injection dosage until stable drug effects are achieved. Monitor for signs of opioid withdrawal.
Examples: | Macrolide antibiotics (e.g., erythromycin), azole-antifungal agents (e.g. ketoconazole), protease inhibitors (e.g., ritonavir), grapefruit juice
CYP3A4 Inducers
Clinical Impact: | The concomitant use of Sufentanil Citrate Injection and CYP3A4 inducers can decrease the plasma concentration of sufentanil [see Clinical Pharmacology (12.3)], resulting in decreased efficacy or onset of a withdrawal syndrome in patients who have developed physical dependence to sufentanil [see Warnings and Precautions (5.4)]. After stopping a CYP3A4 inducer, as the effects of the inducer decline, the sufentanil plasma concentration will increase [see Clinical Pharmacology (12.3)], which could increase or prolong both the therapeutic effects and adverse reactions, and may cause serious respiratory depression.
Intervention: | If concomitant use is necessary, consider increasing the Sufentanil Citrate Injection dosage until stable drug effects are achieved. Monitor for signs of opioid withdrawal. If a CYP3A4 inducer is discontinued, consider Sufentanil Citrate Injection dosage reduction and monitor for signs of respiratory depression.
Examples: | Rifampin, carbamazepine, phenytoin
Benzodiazepines and Other Central Nervous System (CNS) Depressants
Clinical Impact: | The concomitant use of Sufentanil Citrate Injection with CNS depressants my result in decreased pulmonary artery pressure and may cause hypotension. Even small dosages of diazepam may cause cardiovascular depression when added to high dose or anesthetic dosages of Sufentanil Citrate Injection. As postoperative analgesia, concomitant use of Sufentanil Citrate Injection can increase the risk of hypotension, respiratory depression, profound sedation, coma, and death.
Intervention: | As postoperative analgesia, start with a lower dose of Sufentanil Citrate Injection and monitor patients for signs of respiratory depression, sedation, and hypotension. Fluids or other measures to counter hypotension should be available. [see Warnings and Precautions (5.5)].
Examples: | Benzodiazepines and other sedatives/hypnotics, anxiolytics, tranquilizers, muscle relaxants, general anesthetics, antipsychotics, other opioids, alcohol.
Serotonergic Drugs
Clinical Impact: | The concomitant use of opioids with other drugs that affect the serotonergic neurotransmitter system has resulted in serotonin syndrome [see Warnings and Precautions 5.5].
Intervention: | If concomitant use is warranted, carefully observe the patient, particularly during treatment initiation and dose adjustment. Discontinue Sufentanil Citrate Injection if serotonin syndrome is suspected.
Examples: | Selective serotonin reuptake inhibitors (SSRIs), serotonin and norepinephrine reuptake inhibitors (SNRIs), tricyclic antidepressants (TCAs), triptans, 5-HT3 receptor antagonists, drugs that effect the serotonin neurotransmitter system (e.g., mirtazapine, trazodone, tramadol), certain muscle relaxants (i.e., cyclobenzaprine, metaxalone), monoamine oxidase (MAO) inhibitors (those intended to treat psychiatric disorders and also others, such as linezolid and intravenous methylene blue).
Monoamine Oxidase Inhibitors
Clinical Impact: | MAOI interactions with opioids may manifest as serotonin syndrome or opioid toxicity (e.g., respiratory depression, coma) [see Warnings and Precautions (5.2)].
Intervention: | The use of Sufentanil Citrate Injection is not recommended for patients taking MAOIs or within 14 days of stopping such treatment.
Examples: | phenelzine, tranylcypromine, linezolid
Mixed Agonist/Antagonist and Partial Agonist Opioid Analgesics
Clinical Impact: | May reduce the analgesic effect of Sufentanil Citrate Injection and/or precipitate withdrawal symptoms.
Intervention: | Avoid concomitant use.
Examples: | butorphanol, nalbuphine, pentazocine, buprenorphine
Muscle Relaxants
Clinical Impact: | Sufentanil may enhance the neuromuscular blocking action of skeletal muscle relaxants and produce an increased degree of respiratory depression.
Intervention: | Monitor patients for signs of respiratory depression that may be greater than otherwise expected and decrease the dosage of Sufentanil Citrate Injection and/or the muscle relaxant as necessary.
Diuretics
Clinical Impact: | Opioids can reduce the efficacy of diuretics by inducing the release of antidiuretic hormone.
Intervention: | Monitor patients for signs of diminished diuresis and/or effects on blood pressure and increase the dosage of the diuretic as needed.
Anticholinergic Drugs
Clinical Impact: | The concomitant use of anticholinergic drugs may increase risk of urinary retention and/or severe constipation, which may lead to paralytic ileus.
Intervention: | Monitor patients for signs of urinary retention or reduced gastric motility when Sufentanil Citrate Injection is used concomitantly with anticholinergic drugs.
Nitrous oxide
Clinical Impact: | Nitrous oxide has been reported to produce cardiovascular depression when given with higher doses of Sufentanil Citrate Injection.
Intervention: | Monitor patients for signs of cardiovascular depression that may be greater than otherwise expected.

8 USE IN SPECIFIC POPULATIONS

8.1 Pregnancy

Risk Summary

Prolonged use of opioid analgesics during pregnancy may cause neonatal opioid withdrawal syndrome. Available data with Sufentanil Citrate Injection in pregnant women are insufficient to inform a drug-associated risk for major birth defects and miscarriage.

In animal reproduction studies, embryolethality and maternal toxicity were noted in rabbits when sufentanil was administered intravenously at 0.9 times the human procedural dose of 30 mcg/kg during organogenesis. Decreased live fetuses and pup survival were noted in rats treated with sufentanil late in gestation and throughout lactation at doses below the human procedural dose. No malformations were observed in either rats or rabbits at doses below the human procedural dose [see Data].

The estimated background risk of major birth defects and miscarriage for the indicated population is unknown. All pregnancies have a background risk of birth defect, loss, or other adverse outcomes. In the U.S. general population, the estimated background risk of major birth defects and miscarriage in clinically recognized pregnancies is 2 to 4% and 15 to 20%, respectively.

Clinical Considerations

Fetal/Neonatal Adverse Reactions

Prolonged use of opioid analgesics during pregnancy for medical or nonmedical purposes can result in physical dependence in the neonate and neonatal opioid withdrawal syndrome shortly after birth.

Neonatal opioid withdrawal syndrome presents as irritability, hyperactivity and abnormal sleep pattern, high pitched cry, tremor, vomiting, diarrhea and failure to gain weight. The onset, duration, and severity of neonatal opioid withdrawal syndrome vary based on the specific opioid used, duration of use, timing and amount of last maternal use, and rate of elimination of the drug by the newborn. Observe newborns for symptoms of neonatal opioid withdrawal syndrome and manage accordingly [see Warnings and Precautions (5.3)].

Labor or Delivery

Opioids cross the placenta and may produce respiratory depression and psycho-physiologic effects in neonates. An opioid antagonist, such as naloxone, must be available for reversal of opioid-induced respiratory depression in the neonate. Sufentanil Citrate Injection is not recommended for use in pregnant women during or immediately prior to labor, when other analgesic techniques are more appropriate. Opioid analgesics, including Sufentanil Citrate Injection, can prolong labor through actions which temporarily reduce the strength, duration, and frequency of uterine contractions. However, this effect is not consistent and may be offset by an increased rate of cervical dilation, which tends to shorten labor. Monitor neonates exposed to opioid analgesics during labor for signs of excess sedation and respiratory depression.

The use of epidurally administered sufentanil in combination with bupivacaine 0.125% with or without epinephrine is indicated for labor and delivery. Sufentanil is not recommended for intravenous use or for use of larger epidural doses during labor and delivery because of potential risks to the newborn infant after delivery. In clinical trials, one case of severe fetal bradycardia associated with maternal hypotension was reported within 8 minutes of maternal administration of sufentanil 15 mcg plus bupivacaine 0.125% (10 mL total volume).

Data

Animal Data

Pregnant rats were treated with intravenous sufentanil doses of 0.005, 0.02, or 0.08 mg/kg/day (0.03, 0.1, or 0.4 times the human total procedural dose of 30 mcg/kg based on body surface area, respectively). No malformations or embryotoxic effects were noted despite maternal toxicity (increased mortality in the mid- and high-dose group).

Pregnant rabbits were treated with intravenous sufentanil doses of 0.005, 0.02, or 0.08 mg/kg/day (0.05, 0.2, or 0.9 times the human total procedural dose of 30 mcg/kg based on body surface area, respectively). Decreased live fetuses per litter and decreased litter size in the high dose group were noted in the presence of maternal toxicity (decreased body weight gain and mortality in the high-dose group).

No evidence of malformations or adverse effects on the fetus was reported in a published study in which pregnant rats were administered 10, 50, or 100 mcg/kg/day sufentanil (0.05, 0.27, or 0.54 times the human procedural dose of 30 mcg/kg/day based on body surface area) continuously from Gestation Day 5 through Gestation Day 20 via subcutaneously implanted osmotic minipumps.

Pregnant rats were treated intravenously with sufentanil 0.005, 0.02, or 0.08 mg/kg/day (0.03, 0.1, or 0.4 times the human total procedural dose of 30 mcg/day based on body surface area, respectively) from Gestation Day 16 through Lactation Day 21. Sufentanil reduced birth weights in the mid- and high-dose groups, decreased live fetuses in the high-dose group, and decreased pup survival in all groups in the presence of maternal toxicity (decreased weight gain and increased mortality in all groups).

8.2 Lactation

Risk Summary

The developmental and health benefits of breastfeeding should be considered along with the mother's clinical need for Sufentanil Citrate Injection and any potential adverse effects on the breastfed infant from Sufentanil Citrate Injection or from the underlying maternal condition.

Clinical Considerations

Infants exposed to Sufentanil Citrate Injection through breast milk should be monitored for excess sedation and respiratory depression. Withdrawal symptoms can occur in breastfed infants when maternal administration of an opioid analgesic is stopped, or when breastfeeding is stopped.

8.3 Females and Males of Reproductive Potential

Infertility

Chronic use of opioids may cause reduced fertility in females and males of reproductive potential. It is not known whether these effects on fertility are reversible [see Adverse Reactions (6.2)].

8.4 Pediatric Use

The safety and efficacy of intravenous sufentanil in pediatric patients as young as 1 day old undergoing cardiovascular surgery have been documented in a limited number of cases. The clearance of sufentanil in healthy neonates is approximately one-half that in adults and children. The clearance rate of sufentanil can be further reduced by up to a third in neonates with cardiovascular disease, resulting in an increase in the elimination half-life of the drug.

8.5 Geriatric Use

Elderly patients (aged 65 years or older) may have increased sensitivity to sufentanil. In general, use caution when selecting a dosage for an elderly patient, usually starting at the low end of the dosing range, reflecting the greater frequency of decreased hepatic, renal, or cardiac function and of concomitant disease or other drug therapy.

Respiratory depression is the chief risk for elderly patients treated with opioids, and has occurred after large initial doses were administered to patients who were not opioid-tolerant or when opioids were co-administered with other agents that depress respiration. Titrate the dosage of Sufentanil Citrate Injection slowly in geriatric patients and monitor closely for signs of central nervous system and respiratory depression [see Warnings and Precautions (5.6)].

8.6 Hepatic Impairment

Sufentanil Citrate Injection should be administered with caution to patients with liver dysfunction because of the extensive hepatic metabolism. Reduce the dosage as needed and monitor closely for signs of respiratory depression, sedation, and hypotension.

8.7 Renal Impairment

Sufentanil Citrate Injection should be administered with caution to patients with kidney dysfunction because of the renal excretion of sufentanil citrate and its metabolites. Reduce the dosage as needed and monitor for signs of respiratory depression, sedation, and hypotension.

9 DRUG ABUSE AND DEPENDENCE

9.1 Controlled Substance

Sufentanil Citrate Injection contains sufentanil, a Schedule II controlled substance.

9.2 Abuse

Sufentanil Citrate Injection contains sufentanil, a substance with a high potential for abuse similar to other opioids including hydrocodone, hydromorphone, methadone, morphine, oxycodone, oxymorphone, and tapentadol. Sufentanil Citrate Injection can be abused and is subject to misuse, addiction, and criminal diversion [see Warnings and Precautions (5.1)].

Drug addiction is a cluster of behavioral, cognitive, and physiological phenomena that develop after repeated substance use and includes:

a strong desire to take the drug, difficulties in controlling its use, persisting in its use despite harmful consequences, a higher priority given to drug use than to other activities and obligations, increased tolerance, and sometimes a physical withdrawal.

Sufentanil Citrate Injection, like other opioids, can be diverted for non-medical use into illicit channels of distribution. Careful recordkeeping of prescribing information, including quantity, frequency, and renewal requests, as required by state and federal law, is strongly advised.

Risks Specific to Abuse of Sufentanil Citrate Injection

Abuse of Sufentanil Citrate Injection poses a risk of overdose and death. The risk is increased with concurrent use of Sufentanil Citrate Injection with alcohol and other central nervous system depressants.

Parenteral drug abuse is commonly associated with transmission of infectious diseases such as hepatitis and HIV.

9.3 Dependence

Both tolerance and physical dependence can develop during chronic opioid therapy. Tolerance is the need for increasing doses of opioids to maintain a defined effect such as analgesia (in the absence of disease progression or other external factors). Tolerance may occur to both the desired and undesired effects of drugs, and may develop at different rates for different effects.

Physical dependence results in withdrawal symptoms after abrupt discontinuation or a significant dosage reduction of a drug. Withdrawal also may be precipitated through the administration of drugs with opioid antagonist activity (e.g., naloxone, nalmefene), mixed agonist/antagonist analgesics (pentazocine, butorphanol, nalbuphine), or partial agonists (buprenorphine). Physical dependence may not occur to a clinically significant degree until after several days to weeks of continued opioid usage.

10 OVERDOSAGE

Clinical Presentation

Acute overdose with Sufentanil Citrate Injection can be manifested by respiratory depression, somnolence progressing to stupor or coma, skeletal muscle flaccidity, cold and clammy skin, constricted pupils, and, in some cases, pulmonary edema, bradycardia, hypotension, partial or complete airway obstruction, atypical snoring, and death. Marked mydriasis rather than miosis may be seen with hypoxia in overdose situations [see Clinical Pharmacology (12.2)].

Treatment of Overdose

In case of overdose, priorities are the reestablishment of a patent and protected airway and institution of assisted or controlled ventilation, if needed. Employ other supportive measures (including oxygen and vasopressors) in the management of circulatory shock and pulmonary edema as indicated. Cardiac arrest or arrhythmias will require advanced life-support techniques.

The opioid antagonists, naloxone or nalmefene, are specific antidotes to respiratory depression resulting from opioid overdose. For clinically significant respiratory or circulatory depression secondary to sufentanil overdose, administer an opioid antagonist. Opioid antagonists should not be administered in the absence of clinically significant respiratory or circulatory depression secondary to sufentanil overdose.

Because the duration of opioid reversal is expected to be less than the duration of action of sufentanil in Sufentanil Citrate Injection, carefully monitor the patient until spontaneous respiration is reliably reestablished. If the response to an opioid antagonist is suboptimal or only brief in nature, administer additional antagonist as directed by the product's prescribing information.

In an individual physically dependent on opioids, administration of the recommended usual dosage of the antagonist will precipitate an acute withdrawal syndrome. The severity of the withdrawal symptoms experienced will depend on the degree of physical dependence and the dose of the antagonist administered. If a decision is made to treat serious respiratory depression in the physically dependent patient, administration of the antagonist should be initiated with care and by titration with smaller than usual doses of the antagonist.

11 DESCRIPTION

Sufentanil Citrate Injection, is an opioid agonist, available as a solution containing 50 mcg/mL eq. of sufentanil base, adjusted to pH 3.5 to 6.0. The chemical name is N-[4-(methyoxymethyl)-1-[2-(2-thienyl)ethyl]-4-piperidinyl]-N-phenylpropanamide: 2-hydroxy-1,2,3-propanetricarboxylate (1:1). The molecular weight is 578.68. It has the following chemical structure.

Sufentanil Citrate Injection, is a sterile, non-pyrogenic, preservative free aqueous solution for intravenous or epidural injection.

12 CLINICAL PHARMACOLOGY

12.1 Mechanism of Action

Sufentanil is an opioid agonist. When used in balanced general anesthesia, sufentanil has been reported to be as much as 10 times as potent as fentanyl. When administered intravenously as a primary anesthetic agent with 100% oxygen, sufentanil is approximately 5 to 7 times as potent as fentanyl.

12.2 Pharmacodynamics

Effects on the Central Nervous System

Sufentanil produces respiratory depression by direct action on brain stem respiratory centers. The respiratory depression involves both a reduction in the responsiveness of the brain stem respiratory centers to increases in carbon dioxide tension and to electrical stimulation.

Sufentanil causes miosis, even in total darkness. Pinpoint pupils are a sign of opioid overdose but are not pathognomonic (e.g., pontine lesions of hemorrhagic or ischemic origins may produce similar findings). Marked mydriasis rather than miosis may be seen due to hypoxia in overdose situations.

Effects on the Gastrointestinal Tract and Other Smooth Muscle

Sufentanil causes a reduction in motility associated with an increase in smooth muscle tone in the antrum of the stomach and duodenum. Digestion of food in the small intestine is delayed and propulsive contractions are decreased. Propulsive peristaltic waves in the colon are decreased, while tone may be increased to the point of spasm resulting in constipation. Other opioid-induced effects may include a reduction in biliary and pancreatic secretions, spasm of sphincter of Oddi, and transient elevations in serum amylase.

Effects on the Cardiovascular System

Sufentanil produces peripheral vasodilation which may result in orthostatic hypotension or syncope. Manifestations of histamine release and/or peripheral vasodilation may include pruritus, flushing, red eyes and sweating and/or orthostatic hypotension.

Effects on the Endocrine System

Opioids inhibit the secretion of adrenocorticotropic hormone (ACTH), cortisol, and luteinizing hormone (LH) in humans. They also stimulate prolactin, growth hormone (GH) secretion, and pancreatic secretion of insulin and glucagon [see Adverse Reactions (6.2)].

Chronic use of opioids may influence the hypothalamic-pituitary-gonadal axis, leading to androgen deficiency that may manifest as low libido, impotence, erectile dysfunction, amenorrhea, or infertility. The causal role of opioids in the clinical syndrome of hypogonadism is unknown because the various medical, physical, lifestyle, and psychological stressors that may influence gonadal hormone levels have not been adequately controlled for in studies conducted to date [see Adverse Reactions (6.2)].

Effects on the Immune System

Opioids have been shown to have a variety of effects on components of the immune system in in vitro and animal models. The clinical significance of these findings is unknown. Overall, the effects of opioids appear to be modestly immunosuppressive.

Concentration–Efficacy Relationships

The minimum effective analgesic concentration will vary widely among patients, especially among patients who have been previously treated with potent agonist opioids [see Dosage and Administration (2.1, 2.2)]. The minimum effective analgesic concentration of sufentanil for any individual patient may increase over time due to an increase in pain, the development of a new pain syndrome and/or the development of analgesic tolerance.

Concentration–Adverse Reaction Relationships

There is a relationship between increasing sufentanil plasma concentration and increasing frequency of dose-related opioid adverse reactions such as nausea, vomiting, CNS effects, and respiratory depression. In opioid-tolerant patients, the situation may be altered by the development of tolerance to opioid-related adverse reactions [see Dosage and Administration (2.1, 2.2, 2.3)].

12.3 Pharmacokinetics

Sufentanil Citrate Injection is administered by the intravenous or epidural route. The pharmacokinetics of intravenous sufentanil can be described as a three-compartment model.

Absorption

After epidural administration of incremental doses totaling 5 to 40 mcg sufentanil during labor and delivery, maternal and neonatal sufentanil plasma concentrations were at or near the 0.05 to 0.1 ng/mL limit of detection, and were slightly higher in mothers than in their infants.

Distribution

Plasma protein binding of sufentanil, related to the alpha acid glycoprotein concentration, was approximately 93% in healthy males, 91% in mothers and 79% in neonates. Sufentanil has a distribution time of 1.4 minutes and redistribution time of 17.1 minutes.

Elimination

The elimination half-life is 164 minutes in adults. The elimination half-life of sufentanil is shorter (e.g. 97 +/- 42 minutes) in infants and children, and longer in neonates (e.g. 434 +/- 160 minutes) compared to that of adolescents and adults.

Metabolism

The liver and small intestine are the major sites of biotransformation.

Excretion

Approximately 80% of the administered dose is excreted within 24 hours and only 2% of the dose is eliminated as unchanged drug.

13 NONCLINICAL TOXICOLOGY

13.1 Carcinogenesis, Mutagenesis, Impairment of Fertility

Carcinogenesis

Long-term studies in animals to evaluate the carcinogenic potential of sufentanil have not been conducted.

Mutagenesis

Sufentanil was not genotoxic in the in vitro bacterial reverse mutation assay (Ames assay) or in the in vivo rat bone marrow micronucleous assay.

Impairment of Fertility

Fertility and early embryonic development studies were conducted in male and female rats treated with 0.005, 0.02 or 0.08 mg/kg sufentanil IV for 56 days and 14 days prior to mating through gestation respectively. Increased mortality was noted in all treatment groups. Lower pregnancy rated were noted following treatment of males at doses of 0.02 and 0.08 mg/kg (0.1 and 0.4 times the maximum human total procedural dose of 30 mcg/kg IV, based on a body surface area comparison), suggesting the potential for an adverse effect on fertility in males. Increased resorption of fetuses and reduced litter size was noted in the high dose females (0.4 times the maximum human total procedural dose of 30 mcg/kg IV, based on a body surface area comparison) suggesting the potential for fetotoxicity, likely due to maternal toxicity.

14 CLINICAL STUDIES

Epidural Use in Labor and Delivery

Epidural sufentanil was tested in 340 patients in two (one single-center and one multicenter) double-blind, parallel studies. Doses ranged from 10 to 15 mcg sufentanil and were delivered in a 10 mL volume of 0.125% bupivacaine with and without epinephrine 1:200,000. In all cases sufentanil was administered following a dose of local anesthetic to test proper catheter placement. Since epidural opioids and local anesthetics potentiate each other, these results may not reflect the dose or efficacy of epidural sufentanil by itself.

Individual doses of 10 to 15 mcg sufentanil plus bupivacaine 0.125% with epinephrine provided analgesia during the first stage of labor with a duration of 1 to 2 hours. Onset was rapid (within 10 minutes). Subsequent doses (equal dose) tended to have shorter duration. Analgesia was profound (complete pain relief) in 80% to 100% of patients and a 25% incidence of pruritus was observed. The duration of initial doses of sufentanil plus bupivacaine with epinephrine is approximately 95 minutes, and of subsequent doses, 70 minutes.

There are insufficient data to critically evaluate neonatal neuromuscular and adaptive capacity following recommended doses of maternally administered epidural sufentanil with bupivacaine. However, if larger than recommended doses are used for combined local and systemic analgesia, e.g. after administration of a single dose of 50 mcg epidural sufentanil during delivery, then impaired neonatal adaption to sound and light can be detected for 1 to 4 hours and if a dose of 80 mcg is used impaired neuromuscular coordination can be detected for more than 4 hours.

16 HOW SUPPLIED/STORAGE AND HANDLING

Sufentanil Citrate Injection, USP is a sterile aqueous, preservative-free solution, containing 50 mcg/mL eq. of sufentanil base, for intravenous and epidural use, supplied as:

NDC 17478-050-01 | 1 mL ampules in packages of 10
NDC 17478-050-02 | 2 mL ampules in packages of 10
NDC 17478-050-05 | 5 mL ampules in packages of 10

STORAGE AND HANDLING

Storage: Store at 20° to 25°C (68° to 77°F) [See USP Controlled Room Temperature]. Protect from light.

U.S. Patent No. 3,998,834
MAY 1995, SEPTEMBER 1995

AKORN
Manufactured by: Akorn, Inc.
Lake Forest, IL 60045

SFA0N Rev. 10/19

Principal Display Panel Text for Container Label:

NDC 17478-050-01 1 mL Ampule

Sufentanil Citrate CII

Injection, USP

50 mcg/mL

Sufentanil base Rx only

FOR INTRAVENOUS

AND EPIDURAL USE

Preservative Free

Principal Display Panel Text for Carton Label:

NDC 17478-050-01 10 Ampules (1 mL each)

Sufentanil Citrate CII

Injection, USP

50 mcg/mL

Each mL contains: FOR INTRAVENOUS AND EPIDURAL USE

Sufentanil base 50 mcg/mL.

Rx only Preservative Free Akorn logo